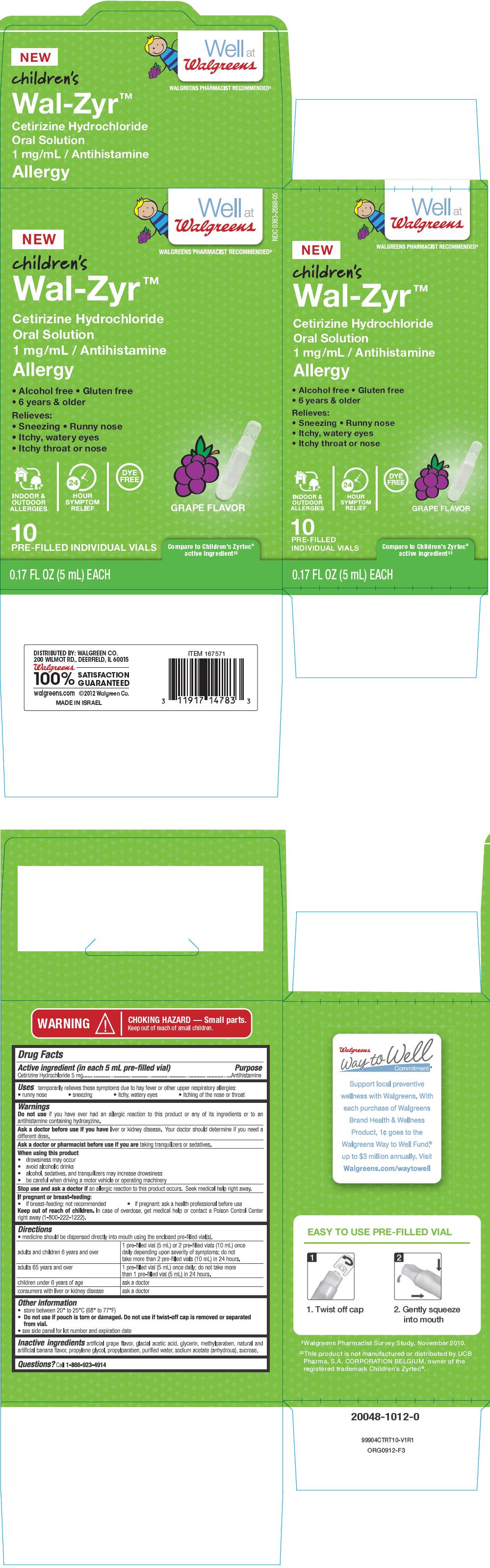 DRUG LABEL: Wal-Zyr 
NDC: 0363-2088 | Form: SOLUTION
Manufacturer: Walgreen Company
Category: otc | Type: HUMAN OTC DRUG LABEL
Date: 20130122

ACTIVE INGREDIENTS: Cetirizine Hydrochloride 5 mg/5 mL
INACTIVE INGREDIENTS: acetic acid; glycerin; methylparaben; propylene glycol; propylparaben; water; sodium acetate anhydrous; sucrose

Wal-Zyr™
Cetirizine Hydrochloride

Drug Facts

Active ingredient (in each 5 mL pre-filled vial)

Cetirizine Hydrochloride 5 mg

Purpose

Antihistamine

Uses

temporarily relieves these symptoms due to hay fever or other upper respiratory allergies:

- runny nose
- sneezing
- itchy, watery eyes
- itching of the nose or throat

Warnings

Do not use if you have ever had an allergic reaction to this product or any of its ingredients or to an antihistamine containing hydroxyzine.

Ask a doctor before use if you have liver or kidney disease. Your doctor should determine if you need a different dose.

Ask a doctor or pharmacist before use if you are taking tranquilizers or sedatives.

When using this product

- drowsiness may occur
- avoid alcoholic drinks
- alcohol, sedatives, and tranquilizers may increase drowsiness
- be careful when driving a motor vehicle or operating machinery

Stop use and ask a doctor if an allergic reaction to this product occurs. Seek medical help right away.

If pregnant or breast-feeding:

- if breast-feeding: not recommended
- if pregnant: ask a health professional before use

Keep out of reach of children. In case of overdose, get medical help or contact a Poison Control Center right away (1-800-222-1222).

Directions

- medicine should be dispensed directly into mouth using the enclosed pre-filled vial(s).

adults and children 6 years and over | 1 pre-filled (5 mL) or 2 pre-filled vials (10 mL) once daily depending upon severity of symptoms; do not take more than 2 pre-filled vials (10 mL) in 24 hours.
adults 65 years and over | 1 pre-filled vial (5 mL) once daily; do not take more than 1 pre-filled vial (5 mL) in 24 hours.
children under 6 years of age | ask a doctor
Consumer with liver or kidney disease | ask a doctor

Other information

- store between 20° to 25°C (68° to 77°F)
- Do not use if pouch is torn or damaged. Do not use if twist-off cap is removed or separated from vial.
- See side panel for lot number and expiration date

Inactive ingredients

artificial grape flavor, glacial acetic acid, glycerin, methylparaben, natural and artificial banana flavor, propylene glycol, propylparaben, purified water, sodium acetate (anhydrous), sucrose.

Questions?

Call 1-866-923-4914

DISTRIBUTED BY: WALGREEN CO.
200 WILMOT RD., DEERFIELD, IL 60015

PRINCIPAL DISPLAY PANEL - 10 Vial Carton

Well at
Walgreens

WALGREENS PHARMACIST RECOMMENDEDǂ

NDC 0363-2088-05

NEW
children's
Wal-Zyr™

Cetirizine Hydrochloride
Oral Solution
1 mg/mL / Antihistamine

Allergy

● Alcohol free ● Gluten free
● 6 years & older

Relieves:

● Sneezing ● Runny nose
● Itchy, watery eyes
● Itchy throat or nose

INDOOR &
OUTDOOR
ALLERGIES

24 HOUR
SYMPTOM
RELIEF

DYE
FREE

GRAPE FLAVOR

10
PRE-FILLED INDIVIDUAL VIALS

Compare to Children's Zyrtec®
active ingredientǂǂ

0.17 FL OZ (5 mL) EACH